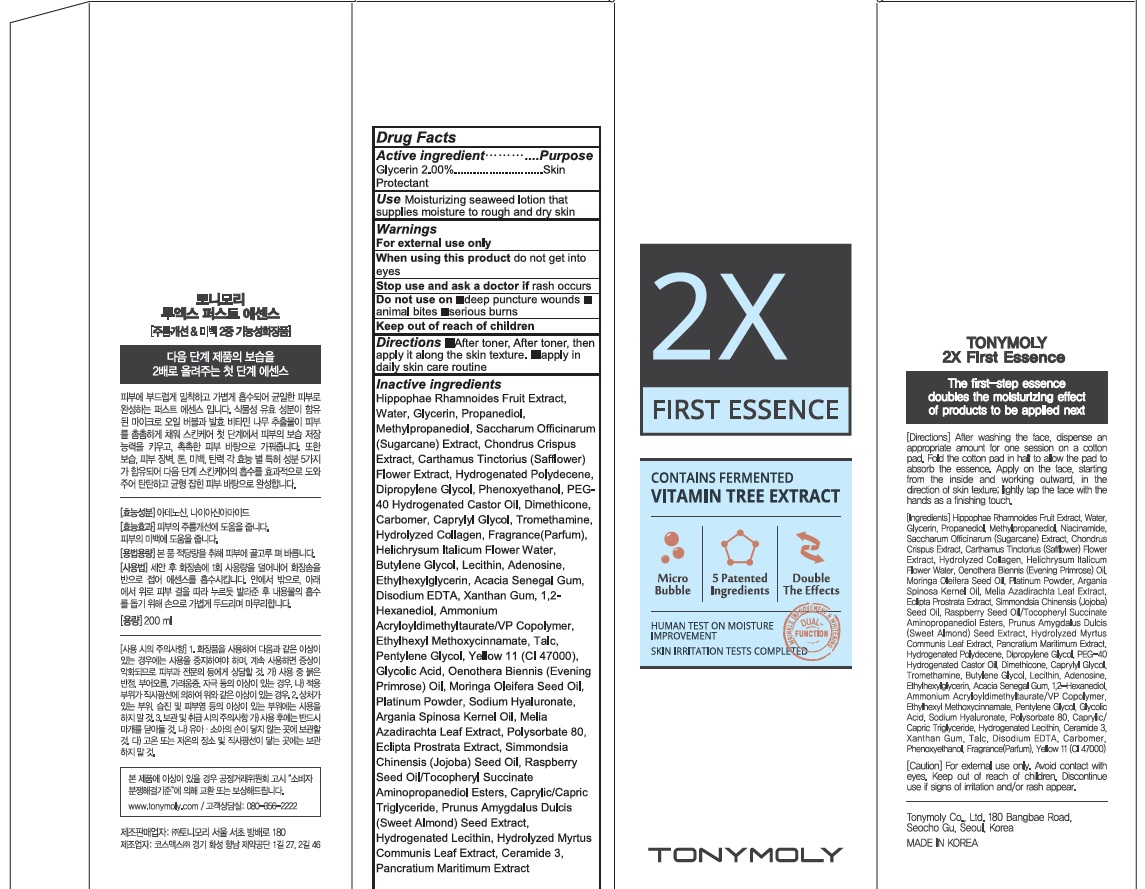 DRUG LABEL: 2X FIRST ESSENCE
NDC: 59078-311 | Form: CREAM
Manufacturer: TONYMOLY CO.,LTD
Category: otc | Type: HUMAN OTC DRUG LABEL
Date: 20160615

ACTIVE INGREDIENTS: Glycerin 4.0 g/200 mL
INACTIVE INGREDIENTS: Water; Propanediol

ACTIVE INGREDIENT

Active ingredient: Glycerin 2.00%

INACTIVE INGREDIENT

Inactive Ingredient: Hippophae Rhamnoides Fruit Extract, Water, Propanediol, Methylpropanediol, Saccharum Officinarum (Sugarcane) Extract, Chondrus Crispus Extract, Carthamus Tinctorius (Safflower) Flower Extract, Hydrogenated Polydecene, Dipropylene Glycol, Phenoxyethanol, PEG-40 Hydrogenated Castor Oil, Dimethicone, Carbomer, Caprylyl Glycol, Tromethamine, Hydrolyzed Collagen, Fragrance(Parfum), Helichrysum Italicum Flower Water, Butylene Glycol, Lecithin, Adenosine, Ethylhexylglycerin, Acacia Senegal Gum, Disodium EDTA, Xanthan Gum, 1,2-Hexanediol, Ammonium Acryloyldimethyltaurate/VP Copolymer, Ethylhexyl Methoxycinnamate, Talc, Pentylene Glycol, Yellow 11 (CI 47000), Glycolic Acid, Oenothera Biennis (Evening Primrose) Oil, Moringa Oleifera Seed Oil, Platinum Powder, Sodium Hyaluronate, Argania Spinosa Kernel Oil, Melia Azadirachta Leaf Extract, Polysorbate 80, Eclipta Prostrata Extract, Simmondsia Chinensis (Jojoba) Seed Oil, Raspberry Seed Oil/Tocopheryl Succinate Aminopropanediol Esters, Caprylic/Capric Triglyceride, Prunus Amygdalus Dulcis (Sweet Almond) Seed Extract, Hydrogenated Lecithin, Hydrolyzed Myrtus Communis Leaf Extract, Ceramide 3, Pancratium Maritimum Extract

PURPOSE

Purpose: Skin Protectant

WARNINGS

Warnings: For external use only. When using this product do not get into eyes. Stop use and ask a doctor if rash occurs. Do not use on - deep puncture wounds - animal bites - serious burns Keep out of reach of children.

KEEP OUT OF REACH OF CHILDREN

Use

Use: Moisturizing seaweed lotion that supplies moisture to rough and dry skin

Directions

Directions: - After toner, After toner, then apply it along the skin texture. - Apply in daily skin care routine